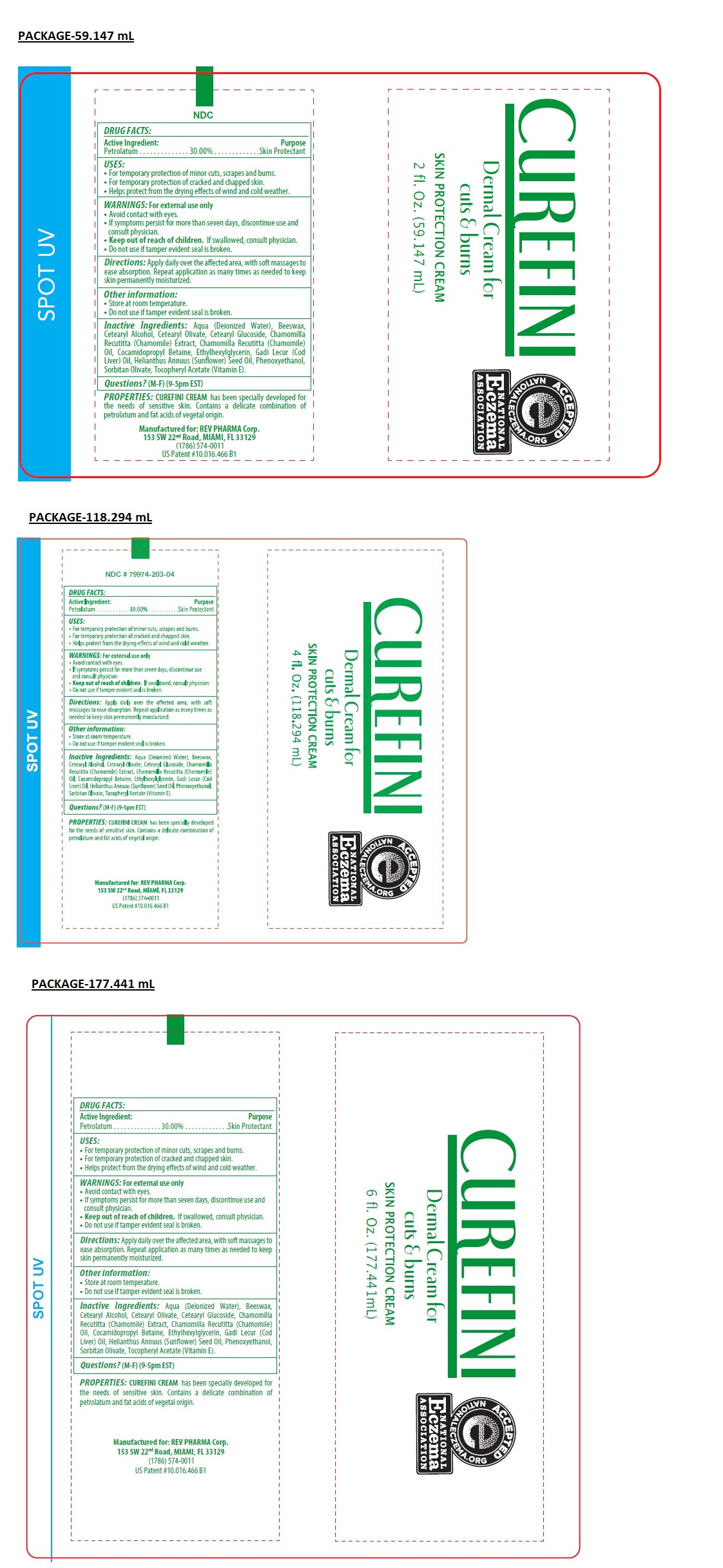 DRUG LABEL: CUREFINI
NDC: 79974-203 | Form: CREAM
Manufacturer: Miramar Cosmetics, Inc DBA Miramar Lab
Category: otc | Type: HUMAN OTC DRUG LABEL
Date: 20241223

ACTIVE INGREDIENTS: PETROLATUM 300 mg/1 mL
INACTIVE INGREDIENTS: WATER; YELLOW WAX; CETOSTEARYL ALCOHOL; CETEARYL OLIVATE; CETEARYL GLUCOSIDE; CHAMOMILE; CHAMOMILE FLOWER OIL; COCAMIDOPROPYL BETAINE; ETHYLHEXYLGLYCERIN; COD LIVER OIL; SUNFLOWER OIL; PHENOXYETHANOL; SORBITAN OLIVATE; .ALPHA.-TOCOPHEROL ACETATE

CUREFINI

Active Ingredient:

Petrolatum.............30.00%

Purpose

Skin Protectant

USES:

• For temporary protection of minor cuts, scrapes and burns.
• For temporary protection of cracked and chapped skin.
• Helps protect from the drying effects of wind and cold weather.

WARNINGS:

For external use only

• Avoid contact with eyes.
• If symptoms persist for more than seven days, discontinue use and consult physician.

• Keep out of reach of children. If swallowed, consult physician.

• Do not use if tamper evident seal is broken.

Directions:

Apply daily over the affected area, with soft massages to ease absorption. Repeat application as many times as needed to keep skin permanently moisturized.

Other information:

• Store at room temperature.
• Do not use if tamper evident seal is broken.

Inactive Ingredients:

Aqua (Deionized Water), Beeswax, Cetearyl Alcohol, Cetearyl Olivate, Cetearyl Glucoside, Chamomilla Recutitta (Chamomile) Extract, Chamomilla Recutitta (Chamomile) Oil, Cocamidopropyl Betaine, Ethylhexylglycerin, Gadi Lecur (Cod Liver) Oil, Helianthus Annuus (Sunflower) Seed Oil, Phenoxyethanol, Sorbitan Olivate, Tocopheryl Acetate (Vitamin E).

Questions?

(M-F) (9-5pm EST)

Dermal Cream for cuts & burns

ACCEPTED NATIONALECZEMA.ORG

NATIONAL ECZEMA ASSOCIATION

PROPERTIES: CUREFINI CREAM has been specially developed for the needs of sensitive skin. Contains a delicate combination of petrolatum and fat acids of vegetal origin.

Manufactured for: REV PHARMA Corp.
153 SW 22nd Road, MIAMI, FL 33129
(1786) 574-0011
US Patent #10.016.466 B1